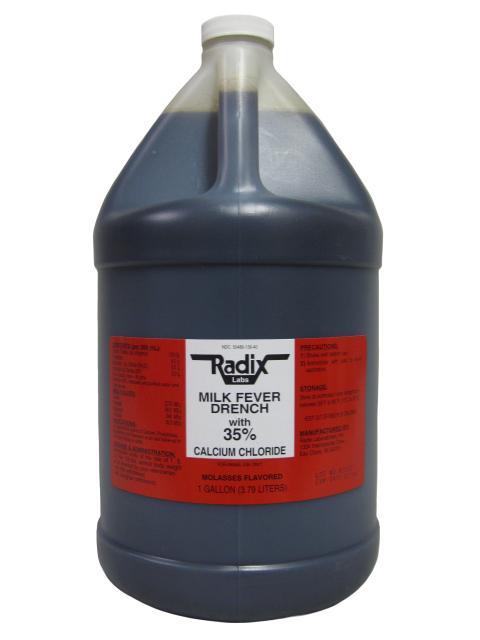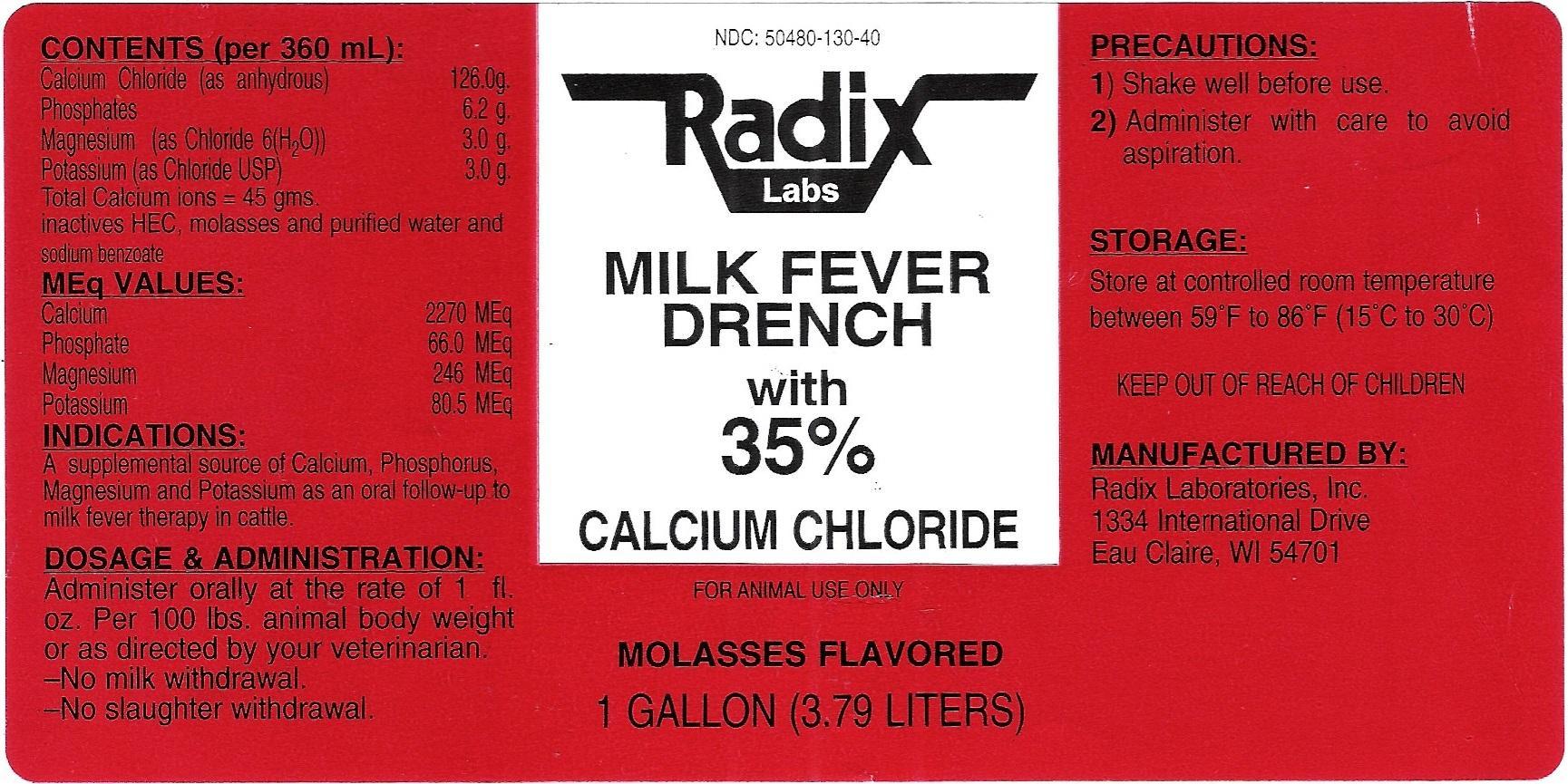 DRUG LABEL: Milk Fever
NDC: 50480-130 | Form: LIQUID
Manufacturer: Radix Laboratories, Inc.
Category: animal | Type: OTC ANIMAL DRUG LABEL
Date: 20141219

ACTIVE INGREDIENTS: CALCIUM CHLORIDE 125 g/360 mL; SODIUM HYPOPHOSPHITE 6.2 g/360 mL; MAGNESIUM CHLORIDE 3.0 g/360 mL; POTASSIUM CHLORIDE 4.5 g/360 mL
INACTIVE INGREDIENTS: Water

Milk Fever

• CONTENTS (per 360ml):

- Calcium Chloride (as anhydrous).........10.0g
- Phosphates........................................6.2g
- Potassium..........................................4.5g
- Magnesium (as Chloride 6 H2O USP).....3.0g
- Total Calcium Ions = 45 gms

• Inactives:

- HEC, Molasses, Purified Water, Sodium Benzoate

• MEq VALUES:

- Calcium..............2252 MEq
- Magnesium...........246 MEq
- Phosphate...........66.0 MEq
- Potassium............120 MEq

INDICATIONS:

- A supplemental source of calcium, phosphorus, magnesium, and potassium as an oral follow-up to milk fever therapy in cattle.

Storage:

- Store at controlled room temperature between 59oF to 86oF (15oC -30oC).

Warning:

- Shake well before use
- Administer with care to avoid aspiration.
- FOR ANIMAL USE ONLY

Dosage and administration:

- Administer orally at the rate of 1 fluid ounce per 100 pounds animal body weight or as directed by your veterinarian.
- No milk withdrawal
- No slaughter withdrawal

- Keep away from children.